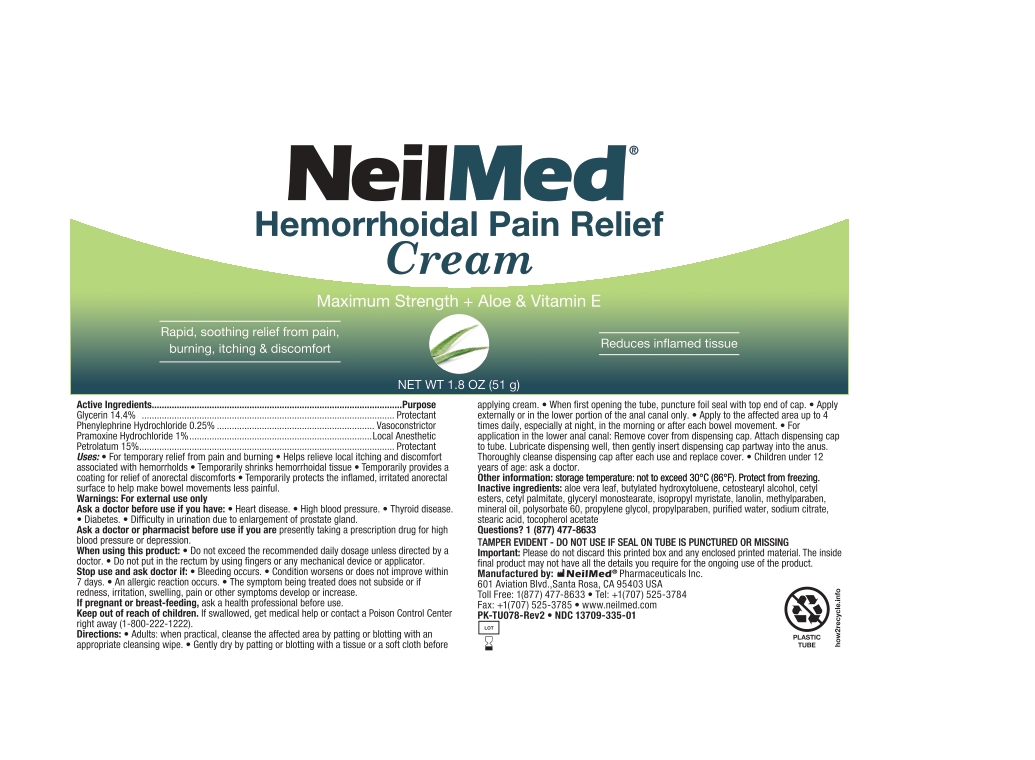 DRUG LABEL: Hemorrhoidal Pain Relief
NDC: 13709-335 | Form: CREAM
Manufacturer: Neilmed Pharmaceuticals Inc.
Category: otc | Type: HUMAN OTC DRUG LABEL
Date: 20250924

ACTIVE INGREDIENTS: PRAMOXINE HYDROCHLORIDE 10 mg/1 g; PHENYLEPHRINE HYDROCHLORIDE 2.5 mg/1 g; GLYCERIN 144 mg/1 g; PETROLATUM 150 mg/1 g
INACTIVE INGREDIENTS: METHYLPARABEN; BUTYLATED HYDROXYTOLUENE; ALPHA-TOCOPHEROL ACETATE; SODIUM CITRATE; CETYL ESTERS; WATER; ISOPROPYL MYRISTATE; POLYSORBATE 60; ALOE VERA LEAF; CETYL PALMITATE; GLYCERYL MONOSTEARATE; MINERAL OIL; PROPYLENE GLYCOL; STEARIC ACID; LANOLIN; PROPYLPARABEN; CETOSTEARYL ALCOHOL

Hemorrhoidal Pain Relief Cream

Drug Facts:

Active Ingredients

Glycerin 14.4%

Phenylephrine HCl 0.25%

Pramoxine HCl 1%

Petrolatum 15%

Drug Facts:

Purpose

Protectant

Vasoconstrictor

Local Anesthetic

Protectant

Uses

- For temporary relief from pain and burning
- Helps relieve local itching and discomfort associated with hemorrhoids
- Temporarily shrinks hemorrhoidal tissue
- Temporarily provides a coating for relief of anorectal discomforts
- Temporarily protects the inflamed, irritated anorectal surface to help make bowel movements less painful

Warnings:

For external use only

Ask a doctor before use if you have:

- Heart disease
- High blood pressure
- Thyroid disease
- Diabetes
- Difficulty in urination due to enlargement of prostate gland

Ask a doctor or pharmacist before use if you are:

Presently taking a prescription drug for high blood pressure or depression.

When using this product:

- Do not exceed the recommended daily dosage unless directed by a doctor.
- Do not put in the rectum by using fingers or any mechanical device or applicator.

Stop use and ask doctor if:

- Bleeding occurs
- Condition worsens or does not improve within 7 days
- An allergic reaction occurs
- The symptom being treated does not subside or if redness, irritation, swelling, pain or other symptoms develop or increase

If pregnant or breast-feeding,

Ask a health professional before use.

Keep out of reach of children.

If swallowed, get medical help or contact a Poison Control Center right away. (1-800-222-1222)

Directions:

- Adults: When practical, cleanse the affected area by patting or blotting with an appropriate cleansing wipe.
- Gently dry by patting or blotting with a tissue or a soft cloth before applying cream.
- When first opening the tube, puncture foil seal with top end of cap.
- Apply externally or in the lower portion of the anal canal only.
- Apply to the affected area up to 4 times daily, especially at night, in the morning or after each bowel movement.
- For application in the lower anal canal: Remove cover from dispensing cap. Attach dispensing cap to tube. Lubricate dispensing cap well using cream from the tube, then gently insert dispensing cap partway into anus. Thoroughly cleanse dispensing cap after each use and replace cover.
- Children under 12 years of age: ask a doctor.

Other information:

storage temperature: not to exceed 30°C (86°F). Protect from freezing.

Inactive ingredients:

Aloe vera leaf, butylated hydroxytoluene, cetostearyl alcohol, cetyl esters, cetyl palmitate, glyceryl monostearate, isopropyl myristate, lanolin, methylparaben, mineral oil, polysorbate 60, propylene glycol, propylparaben, purified water, sodium citrate, stearic acid, tocopherol acetate

Questions or comments?

1 (877) 477-8633

TAMPER EVIDENT: DO NOT USE IF SEAL ON TUBE IS PUNCTURED OR MISSING

Important:

Please do not discard this printed box and any enclosed printed material.
The inside final product may not have all the details you require for the ongoing use of the product.